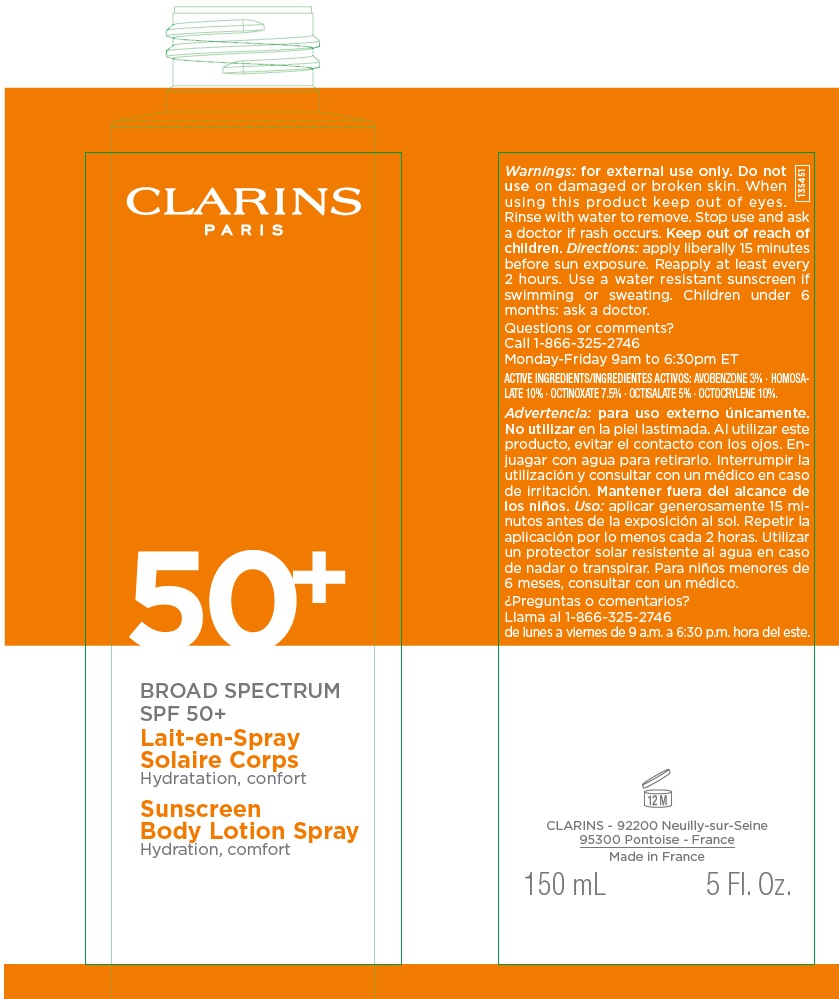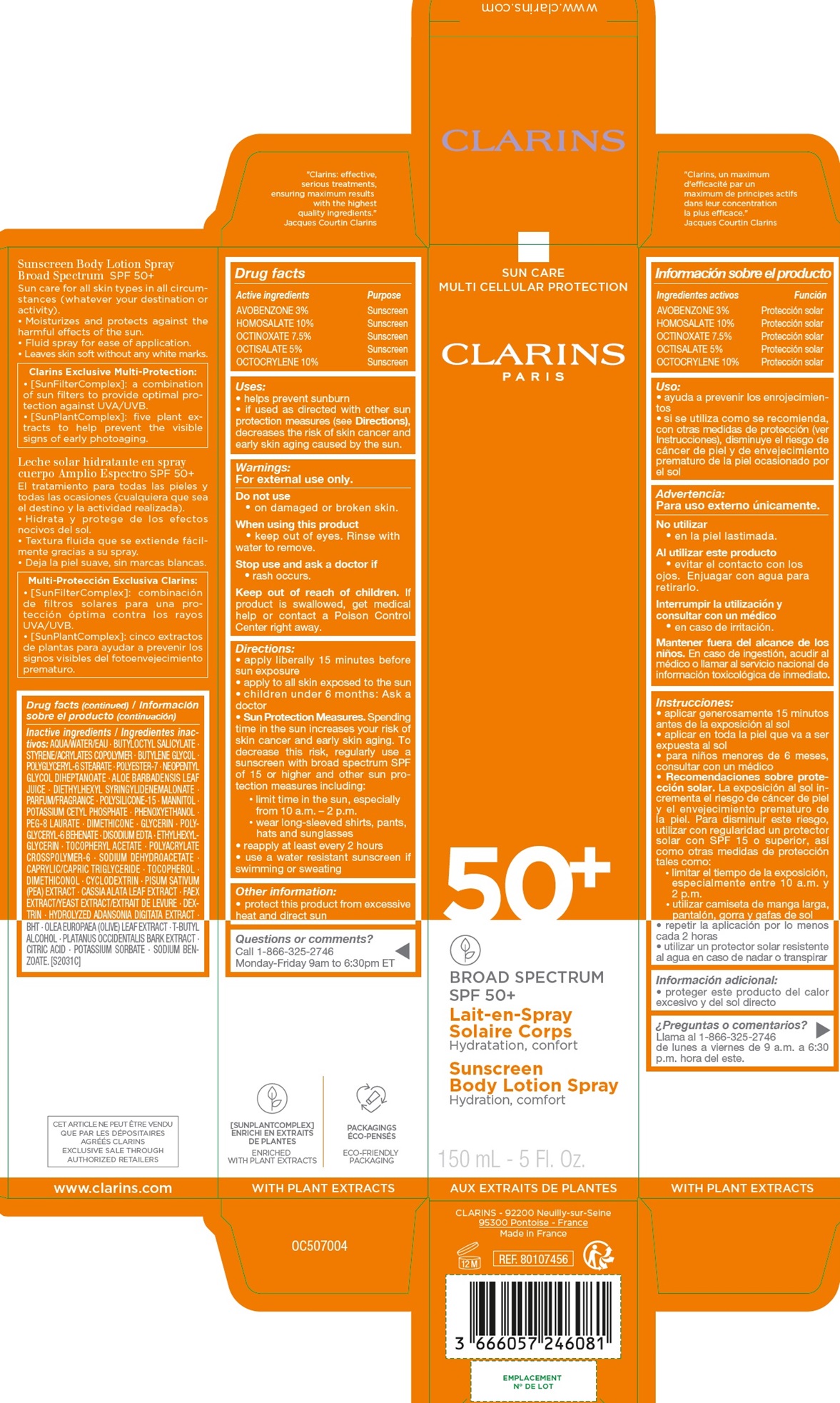 DRUG LABEL: CLARINS BROAD SPECTRUM SPF 50 Sunscreen Body
NDC: 58668-9922 | Form: CREAM
Manufacturer: Laboratoires Clarins
Category: otc | Type: HUMAN OTC DRUG LABEL
Date: 20231206

ACTIVE INGREDIENTS: AVOBENZONE 30 mg/1 mL; HOMOSALATE 100 mg/1 mL; OCTINOXATE 75 mg/1 mL; OCTISALATE 50 mg/1 mL; OCTOCRYLENE 100 mg/1 mL
INACTIVE INGREDIENTS: WATER; BUTYLOCTYL SALICYLATE; STYRENE; BUTYLENE GLYCOL; POLYGLYCERYL-6 STEARATE; POLYESTER-7; NEOPENTYL GLYCOL DIHEPTANOATE; ALOE VERA LEAF; DIETHYLHEXYL SYRINGYLIDENEMALONATE; POLYSILICONE-15; MANNITOL; POTASSIUM CETYL PHOSPHATE; PHENOXYETHANOL; PEG-8 LAURATE; DIMETHICONE; GLYCERIN; POLYGLYCERYL-6 BEHENATE; EDETATE DISODIUM ANHYDROUS; ETHYLHEXYLGLYCERIN; .ALPHA.-TOCOPHEROL ACETATE; AMMONIUM ACRYLOYLDIMETHYLTAURATE, DIMETHYLACRYLAMIDE, LAURYL METHACRYLATE AND LAURETH-4 METHACRYLATE COPOLYMER, TRIMETHYLOLPROPANE TRIACRYLATE CROSSLINKED (45000 MPA.S); SODIUM DEHYDROACETATE; MEDIUM-CHAIN TRIGLYCERIDES; TOCOPHEROL; CYCLODEXTRINS; PEA; SENNA ALATA LEAF; YEAST, UNSPECIFIED; BUTYLATED HYDROXYTOLUENE; OLEA EUROPAEA LEAF; TERT-BUTYL ALCOHOL; PLATANUS OCCIDENTALIS BARK; CITRIC ACID MONOHYDRATE; POTASSIUM SORBATE; SODIUM BENZOATE

CLARINS - BROAD SPECTRUM SPF 50+ Sunscreen Body Lotion Spray

Active ingredients

AVOBENZONE 3%,

HOMOSALATE 10%,

OCTINOXATE 7.5%,

OCTISALATE 5%,

OCTOCRYLENE 10%

Purpose

Sunscreen

Uses:

• helps prevent sunburn • if used as directed with other sun protection measures (see

Directions)

, decreases the risk of skin cancer and early skin aging caused by the sun.

Warnings:

For external use only.

Do not use

• on damaged or broken skin.

When using this product

• keep out of eyes. Rinse with water to remove.

Stop use and ask a doctor if

• rash occurs.

Keep out of reach of children.

If product is swallowed, get medical help or contact a Poison Control Center right away.

Directions:

• apply liberally 15 minutes before sun exposure • apply to all skin exposed to the sun • children under 6 months: Ask a doctor

• Sun Protection Measures.

Spending time in the sun increases your risk of skin cancer and early skin aging. To decrease this risk, regularly use a sunscreen with broad spectrum SPF of 15 or higher and other sun protection measures including: • limit time in the sun, especially from 10 a.m. – 2 p.m. • wear long-sleeved shirts, pants, hats and sunglasses • reapply at least every 2 hours • use a water resistant sunscreen if swimming or sweating

Other information:

• protect this product from excessive heat and direct sun

Questions or comments?

Call 1-866-325-2746 Monday-Friday 9am to 6:30pm ET

Inactive ingredients

AQUA/WATER/EAU . BUTYLOCTYL SALICYLATE . STYRENE/ACRYLATES COPOLYMER . BUTYLENE GLYCOL . POLYGLYCERYL-6 STEARATE . POLYESTER-7 . NEOPENTYL GLYCOL DIHEPTANOATE . ALOE BARBADENSIS LEAF JUICE . DIETHYLHEXYL SYRINGYLIDENEMALONATE . PARFUM/FRAGRANCE . POLYSILICONE-15 . MANNITOL . POTASSIUM CETYL PHOSPHATE . PHENOXYETHANOL . PEG-8 LAURATE . DIMETHICONE . GLYCERIN . POLYGLYCERYL- 6 BEHENATE . DISODIUM EDTA . ETHYLHEXYLGLYCERIN . TOCOPHERYL ACETATE . POLYACRYLATE CROSSPOLYMER-6 . SODIUM DEHYDROACETATE . CAPRYLIC/CAPRIC TRIGLYCERIDE . TOCOPHEROL . DIMETHICONOL . CYCLODEXTRIN . PISUM SATIVUM (PEA) EXTRACT . CASSIA ALATA LEAF EXTRACT . FAEX EXTRACT/YEAST EXTRACT/EXTRAIT DE LEVURE . DEXTRIN . HYDROLYZED ADANSONIA DIGITATA EXTRACT . BHT . OLEA EUROPAEA (OLIVE) LEAF EXTRACT . T-BUTYL ALCOHOL . PLATANUS OCCIDENTALIS BARK EXTRACT . CITRIC ACID . POTASSIUM SORBATE . SODIUM BENZOATE. [S2031C]